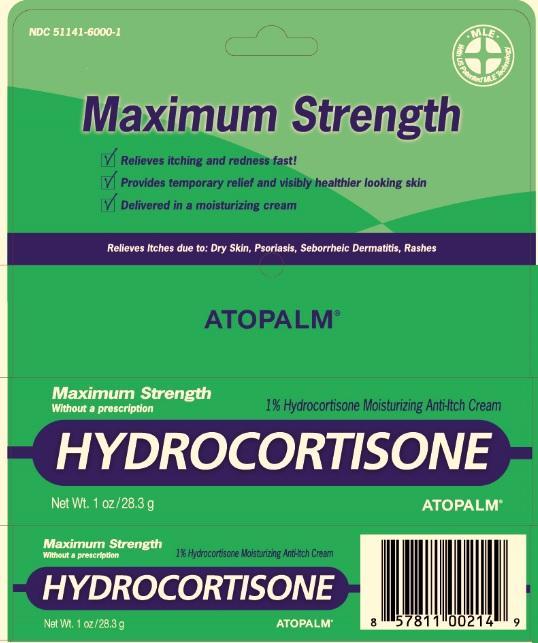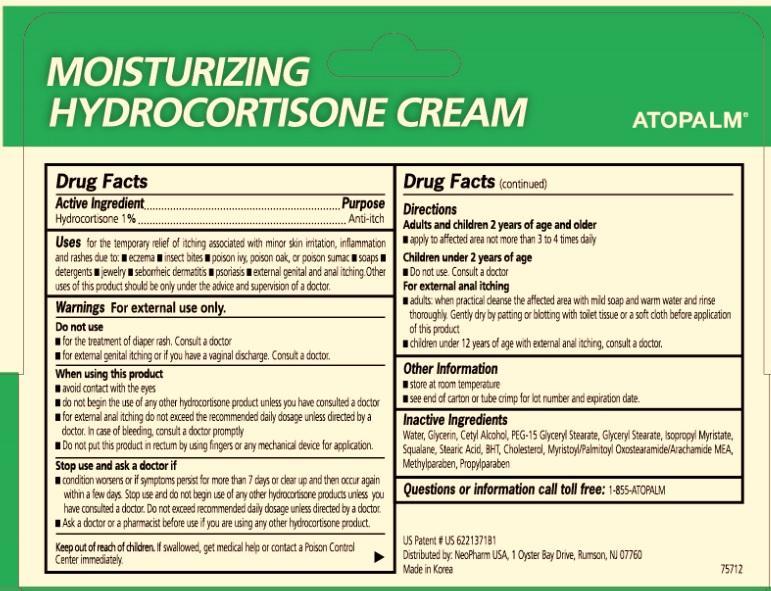 DRUG LABEL: ATOPALM Moisturizing Hydrocortisone
                        
NDC: 51141-6000 | Form: CREAM
Manufacturer: NeoPharm Co., Ltd.
Category: otc | Type: HUMAN OTC DRUG LABEL
Date: 20150609

ACTIVE INGREDIENTS: HYDROCORTISONE 1 g/100 g
INACTIVE INGREDIENTS: WATER; GLYCERIN; PEG-15 GLYCERYL STEARATE; ISOPROPYL MYRISTATE; SQUALANE; STEARIC ACID; BUTYLATED HYDROXYTOLUENE; CHOLESTEROL; METHYLPARABEN; PROPYLPARABEN; MYRISTOYL/PALMITOYL OXOSTEARAMIDE/ARACHAMIDE MEA

ATOPALM Moisturizing Hydrocortisone Cream

Active Ingredient
Hydrocortisone 1%

Purpose

Anti-itch

INDICATIONS AND USAGE

Uses for the temporary relief or itching associated with minor skin irritation, inflammation and rashes due to:
eczema
insect bites
poison ivy, poison oak, or poison sumac
soaps
detergents
jewelry
seborrheic dermatitis
psoriasis
external genital and anal itching Other uses of this product should be only under the advice and supervision of a doctor.

Warnings For external use only.

Do not use

for the treatment of diaper rash. Consult a doctor
for external genital itching or if you have a vaginal discharge. Consult a doctor.

When using this product

avoid contact with the eyes
do not begin the use of any other hydrocortisone product unless you have consulted a doctor
for external anal itching do not exceed the recommended daily dosage unless directed by a doctor. In case of bleeding, consult a doctor promptly.
Do not put this product in rectum by using fingers or any mechanical devise for application.

Stop use and ask a doctor if

condition worsens or if symptoms persist for more than 7 days or clean up and then occur again within a few days. Stop use and do not begin use of any other hydrocortisone products unless you have consulted a doctor. Do not exceed recommended daily dosage unless directed by a doctor.

Ask a doctor or a pharmacist before use if you are using any other hydrocortisone product.

Keep out of reach of children. If swallowed, get medical help or contact a Poison Control Center immediately.

Directions

Adults and children 2 years of age and older

apply to affected area not more than 3 to 4 times daily Children under 2 years of age
Do not use. Consult a doctor.
For external anal itching
adults: when practical cleanse the affected area with mild soap and warm water and rinse thoroughly. Gently dry by patting or blotting with toilet tissue or a soft cloth before application of this product.
children under 12 years of age with external anal itching, consult a doctor.

Other Information
store at room temperature
see end of carton or tube crimp for lot number and expiration date

INACTIVE INGREDIENT

Inactive Ingredients Water, Glycerin, Cetyl Alcohol, PEG-15 Glyceryl Stearate, Glyceryl Stearate, Isopropyl Myristate, Squalane, Stearic Acid, BHT, Cholesterol, Myristoyl/Palmitoyl Oxostearamide/ Arachamide MEA, Methylparaben, Propylparaben

Questions? Call 1-855-ATOPALM

US Patent # US 6221371B1 Distributed by: NeoPharm Co., Ltd., 80 Wood Rd., #212 Camarillo, CA 93010 Made in Korea 75712 LOT and EXP.

PACKAGE LABEL

Maximum Strength

plus US Patented Technology

1% Hydrocortisone

ATOPALM TM

MOISTURIZING HYDROCORTISONE CREAM

WITH US PATENTED M L E TECHNOLOGY

Relieves Itching and Redness Fast!

Provides Temporary Relief and Visibly Healthier Looking Skin

Maximum Strength

medicine without a prescription for temporary relief of your worst itch symptoms.

ATOPALM TM
Relieves itches due to: Dry Skin, Psoriasis, Seborrheic Dermatitis, Rashes
Net Wt. 1 oz/ 28.3 g